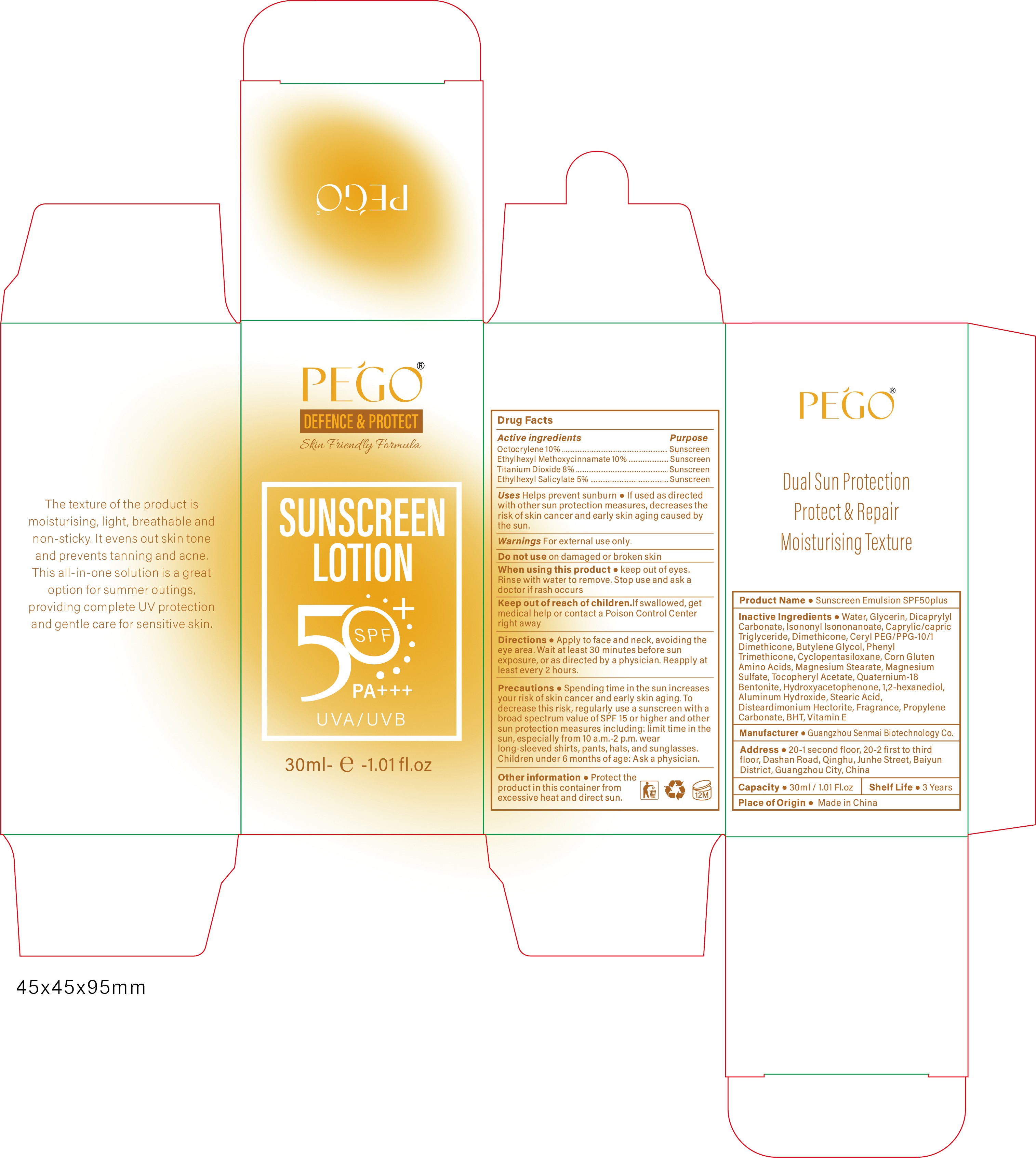 DRUG LABEL: Sunscreen Emulsion SPF50plus
NDC: 84509-002 | Form: LOTION
Manufacturer: Guangzhou Senmai Biotechnology Co.
Category: otc | Type: HUMAN OTC DRUG LABEL
Date: 20250108

ACTIVE INGREDIENTS: OCTISALATE 1500 mg/30 mL; OCTOCRYLENE 3000 mg/30 mL; OCTINOXATE 3000 mg/30 mL; TITANIUM DIOXIDE 2400 mg/30 mL
INACTIVE INGREDIENTS: AMINO ACIDS, CORN GLUTEN; MEDIUM-CHAIN TRIGLYCERIDES; BUTYLENE GLYCOL; PHENYL TRIMETHICONE; 1,2-HEXANEDIOL; ALUMINUM HYDROXIDE; STEARIC ACID; DISTEARDIMONIUM HECTORITE; FRAGRANCE 13576; PROPYLENE CARBONATE; .ALPHA.-TOCOPHEROL; .ALPHA.-TOCOPHEROL ACETATE; GLYCERIN; WATER; DICAPRYLYL CARBONATE; ISONONYL ISONONANOATE; DIMETHICONE; CETYL PEG/PPG-10/1 DIMETHICONE (HLB 5); CYCLOMETHICONE 5; MAGNESIUM SULFATE, UNSPECIFIED; MAGNESIUM STEARATE; BENTOQUATAM; HYDROXYACETOPHENONE; BUTYLATED HYDROXYTOLUENE

Active ingredients

Octocrylene 10%
Ethylhexyl Methoxycirnnamate 10%

Titanium Dioxide 8%
Ethylhexyl Salicylate 5%

Purpose

Sunscreen

Uses

Helps prevent sunburn
lf used as directed with other sun protection measures, decreases the risk of skin cancer and early skin aging caused by the sun.

Warnings

For external use only

Do not use

on damaged or broken skin

When using this product

Keep out of eyes. Rinse with water to remove. Stop and ask a doctor if rash occurs.

Keep out of reach of children.

If swallowed, get medical help or contact a Poison Conirol Center right away

Directions

Apply to face and neck, avoiding the eye area. Wait at least 30 minutes before sun exposure, or as directed by a physician. Reapply at least every 2 hours

Precautions

Spending timein the sun increasesyour risk ofskin cancer and early skin aging.Todecrease this risk, regularly use a sunscreen with abroad spectrum value of SPF 15 or higher and othersun protection measures including: limit time in thsun,especially from 10 a.m.-2 p.m.wearlong-sleeved shirts, pants, hats, and sunglasses.Children under 6 months of age: Ask a physician.

Other information

Protect the product in this container from excessive heat and direct sun.

Product Name

Sunscreen Emulsion SPF50plus

Inactive Ingredients

Water, Glycerin, Dicaprylyl Carbonate, Isononyllsononanoate, Caprylic/capric Triglyceride, Dimethicone, Ceryl PEG/PPG-10/1 Dimethicone, Butylene Glycol, Phenyl Trimethicone,Cyclopentasiloxane,Corn Gluten Amino Acids, Magnesium Stearate,Magnesium Sulfate,Tocopheryl Acetate, Quaternium-18Bentonite, Hydroxyacetophenone, 1,2-hexanediol, Aluminum Hydroxide, Stearic Acid,
Disteardimonium Hectorite,Fragrance,Propylene Carbonate,BHT,Vitamin E

Manufacturer

Guangzhou Senmai Biotechnology Co.

Address

20-1second floor, 20-2 first to third floor,Dashan Road,Qinghu,Junhe Street, Baiyun district, Guangzhou City, China.

Capacity

30ml/1.05 Fl.oz

Shelf Life

3 Years

Place of Origin

Made in China